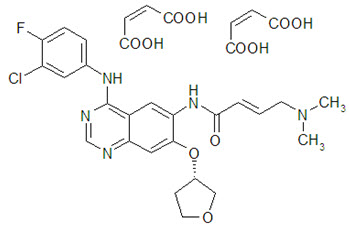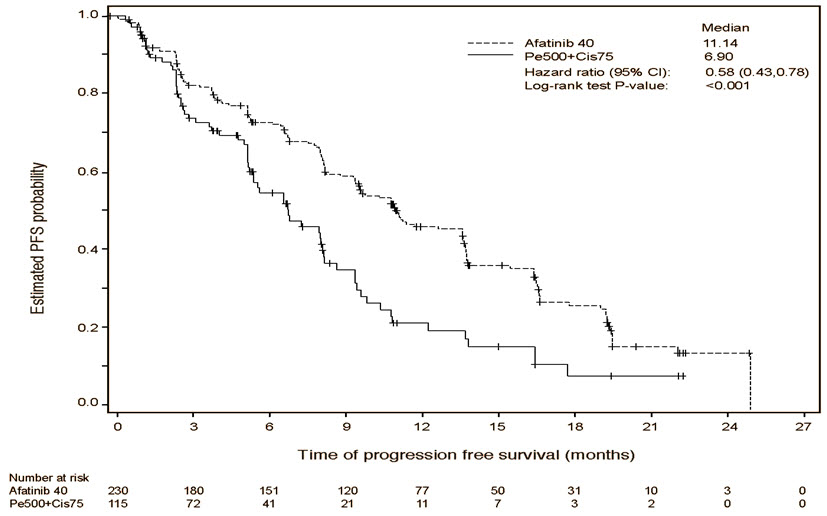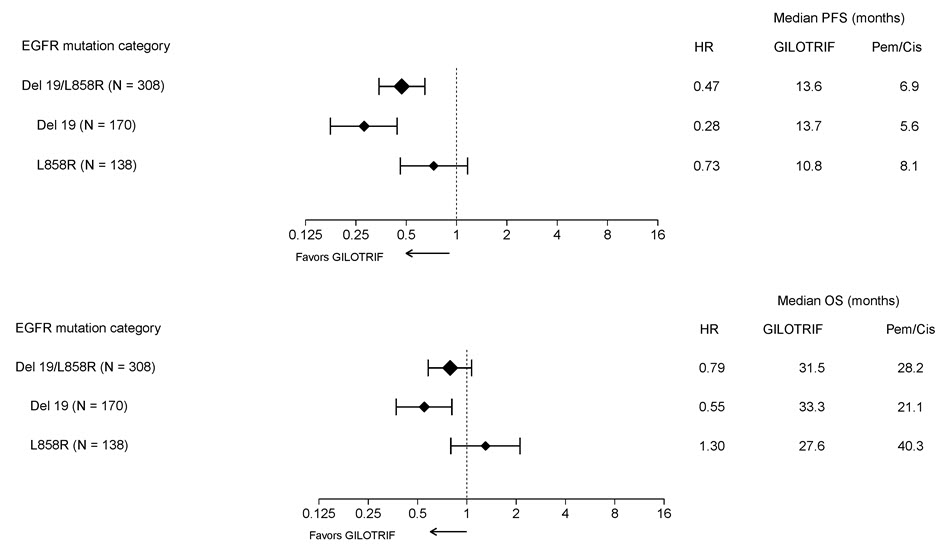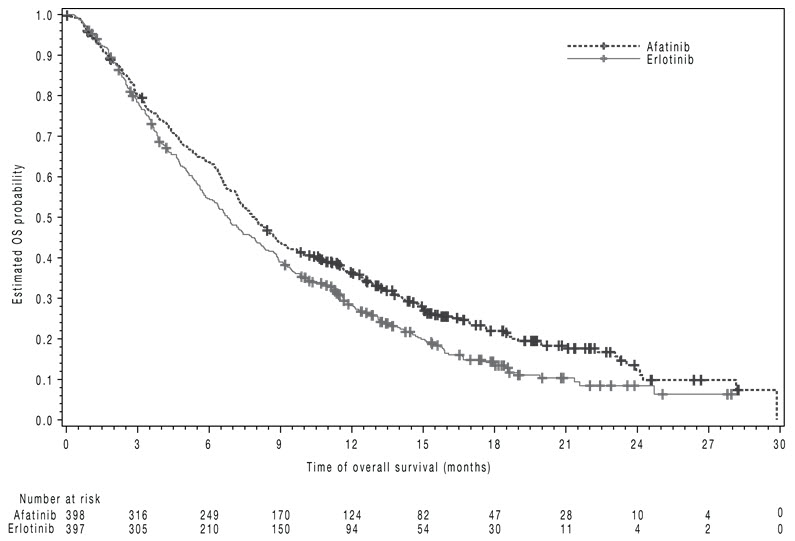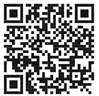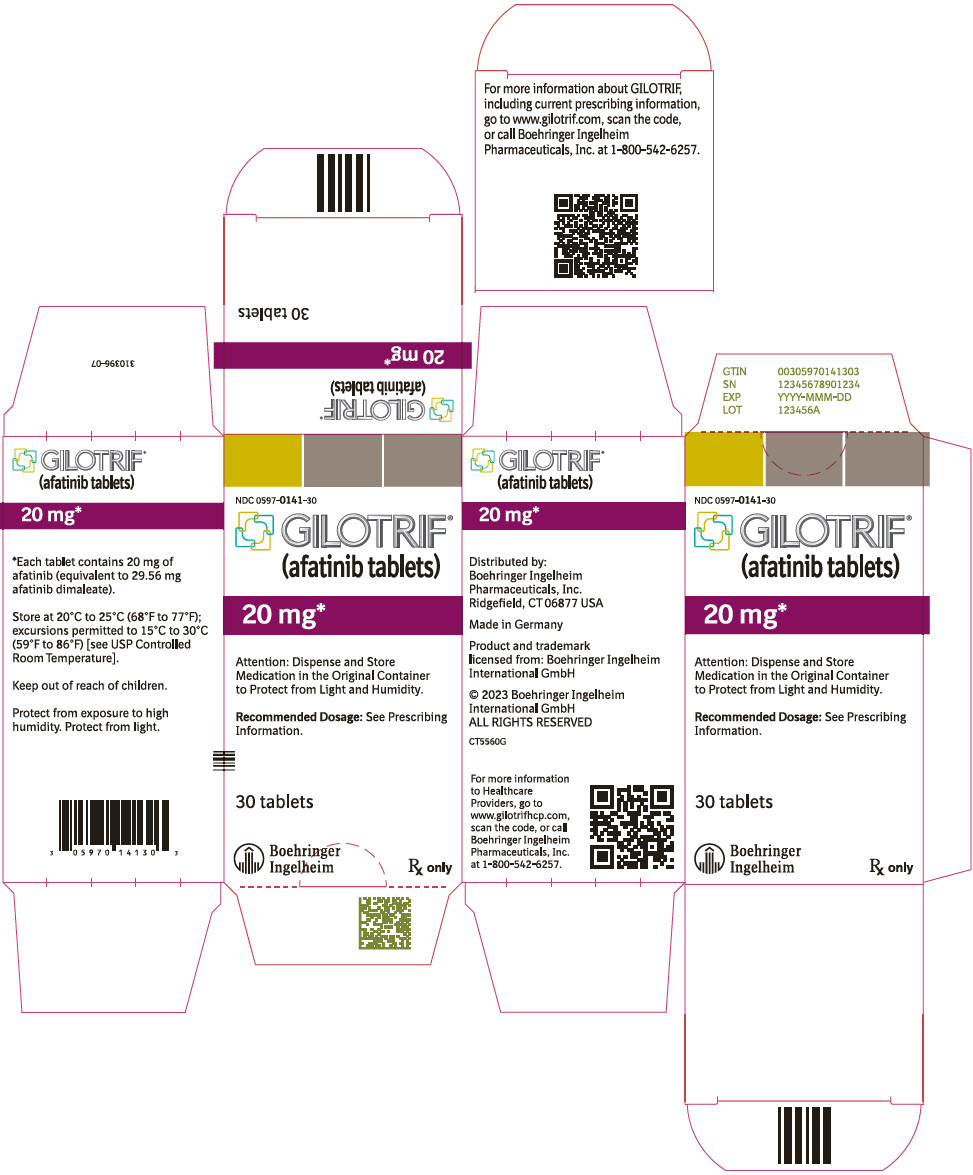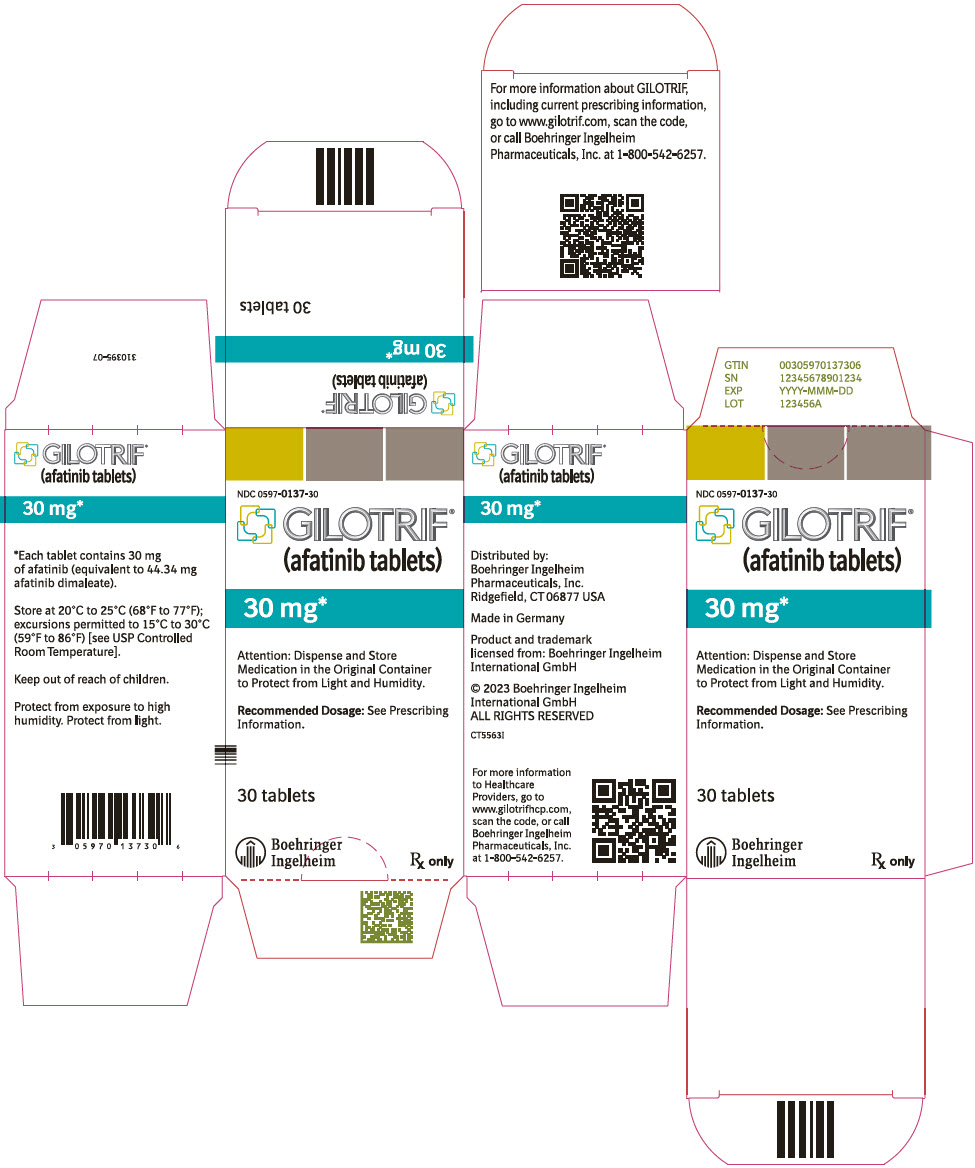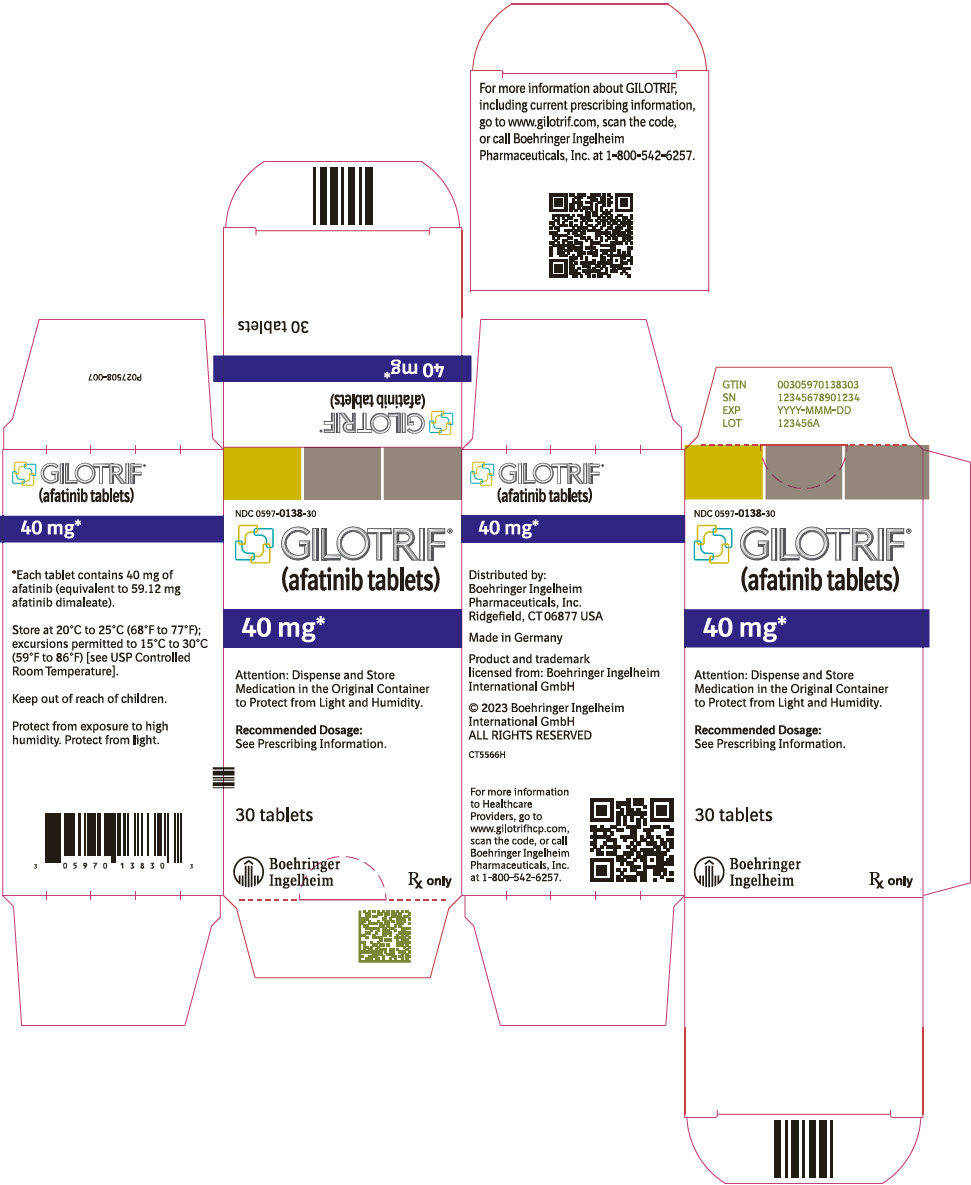 DRUG LABEL: Gilotrif
NDC: 0597-0141 | Form: TABLET, FILM COATED
Manufacturer: Boehringer Ingelheim Pharmaceuticals, Inc.
Category: prescription | Type: HUMAN PRESCRIPTION DRUG LABEL
Date: 20251113

ACTIVE INGREDIENTS: AFATINIB 20 mg/1 1

HIGHLIGHTS OF PRESCRIBING INFORMATION

These highlights do not include all the information needed to use GILOTRIF safely and effectively. See full prescribing information for GILOTRIF.
GILOTRIF® (afatinib tablets), for oral use
Initial U.S. Approval: 2013

1 INDICATIONS AND USAGE

GILOTRIF is a kinase inhibitor indicated for:

- First-line treatment of patients with metastatic non-small cell lung cancer (NSCLC) whose tumors have non-resistant epidermal growth factor receptor (EGFR) mutations as detected by an FDA-approved test (1.1)
  Limitations of Use: Safety and efficacy of GILOTRIF were not established in patients whose tumors have resistant EGFR mutations (1.1)
- Treatment of patients with metastatic, squamous NSCLC progressing after platinum-based chemotherapy (1.2)

2 DOSAGE AND ADMINISTRATION

- Recommended dosage: 40 mg orally once daily (2.2)
- Renal impairment: 30 mg orally once daily in patients with severe renal impairment (2.4, 8.6, 12.3)
- Instruct patients to take GILOTRIF at least 1 hour before or 2 hours after a meal (2.2)

3 DOSAGE FORMS AND STRENGTHS

Tablets: 40 mg, 30 mg, and 20 mg (3)

4 CONTRAINDICATIONS

None. (4)

5 WARNINGS AND PRECAUTIONS

- Diarrhea: Diarrhea may result in dehydration and renal failure. Withhold GILOTRIF for severe and prolonged diarrhea not responsive to anti-diarrheal agents. (2.3, 5.1)
- Bullous and exfoliative skin disorders: Severe bullous, blistering, and exfoliating lesions occurred in 0.2% of patients. Discontinue for life-threatening cutaneous reactions. Withhold GILOTRIF for severe and prolonged cutaneous reactions. (2.3, 5.2)
- Interstitial lung disease (ILD): Occurs in 1.6% of patients. Withhold GILOTRIF for acute onset or worsening of pulmonary symptoms. Discontinue GILOTRIF if ILD is diagnosed. (2.3, 5.3)
- Hepatic toxicity: Fatal hepatic impairment occurs in 0.2% of patients. Monitor with periodic liver testing. Withhold or discontinue GILOTRIF for severe or worsening liver tests. (2.3, 5.4)
- Gastrointestinal perforation: Occurs in 0.2% of patients. Permanently discontinue GILOTRIF in patients who develop gastrointestinal perforation. (2.3, 5.5)
- Keratitis: Occurs in 0.7% of patients. Withhold GILOTRIF for keratitis evaluation. Withhold or discontinue GILOTRIF for confirmed ulcerative keratitis. (2.3, 5.6)
- Embryo-fetal toxicity: Can cause fetal harm when administered to a pregnant woman. Advise pregnant women and females of reproductive potential of the potential risk to the fetus and to use effective contraception. (5.7)

6 ADVERSE REACTIONS

Most common adverse reactions (≥20%) were diarrhea, rash/acneiform dermatitis, stomatitis, paronychia, dry skin, decreased appetite, nausea, vomiting, pruritus (6.1).

To report SUSPECTED ADVERSE REACTIONS, contact Boehringer Ingelheim Pharmaceuticals, Inc. at (800) 542-6257 or FDA at 1-800-FDA-1088 or www.fda.gov/medwatch.

7 DRUG INTERACTIONS

- P-glycoprotein (P-gp) Inhibitors: Co-administration of P-gp inhibitors can increase afatinib exposure. Reduce GILOTRIF by 10 mg per day if not tolerated. (2.5, 7)
- P-gp Inducers: Co-administration of chronic P-gp inducers orally can decrease afatinib exposure. Increase GILOTRIF by 10 mg per day as tolerated. (2.5, 7)

8 USE IN SPECIFIC POPULATIONS

Lactation: Advise women not to breastfeed (8.2)

FULL PRESCRIBING INFORMATION

1 INDICATIONS AND USAGE

1.1 EGFR Mutation-Positive, Metastatic Non-Small Cell Lung Cancer

GILOTRIF is indicated for the first-line treatment of patients with metastatic non-small cell lung cancer (NSCLC) whose tumors have non-resistant epidermal growth factor receptor (EGFR) mutations as detected by an FDA-approved test [see Dosage and Administration (2.1), Clinical Pharmacology (12.1), Clinical Studies (14.1)].

Limitations of Use: The safety and efficacy of GILOTRIF have not been established in patients whose tumors have resistant EGFR mutations [see Clinical Studies (14.1)].

1.2 Previously Treated, Metastatic Squamous NSCLC

GILOTRIF is indicated for the treatment of patients with metastatic squamous NSCLC progressing after platinum-based chemotherapy.

2 DOSAGE AND ADMINISTRATION

2.1 Patient Selection for Non-Resistant EGFR Mutation-Positive Metastatic NSCLC

Select patients for first-line treatment of metastatic NSCLC with GILOTRIF based on the presence of non-resistant EGFR mutations in tumor specimens [see Clinical Pharmacology (12.1), Clinical Studies (14.1)]. Information on FDA-approved tests for the detection of EGFR mutations in NSCLC is available at: http://www.fda.gov/CompanionDiagnostics.

2.2 Recommended Dosage

The recommended dosage of GILOTRIF is 40 mg orally once daily until disease progression or no longer tolerated by the patient.

Take GILOTRIF at least 1 hour before or 2 hours after a meal.

Do not take a missed dose within 12 hours of the next dose.

2.3 Dosage Modifications for Adverse Reactions

Withhold GILOTRIF for:

- Grade* 3 or higher adverse reactions
- Diarrhea of Grade 2 persisting for 2 or more consecutive days while taking anti-diarrheal medication [see Warnings and Precautions (5.1)]
- Cutaneous reactions of Grade 2 that are prolonged (lasting more than 7 days) or intolerable [see Warnings and Precautions (5.2)]

* National Cancer Institute Common Terminology Criteria for Adverse Events (NCI CTCAE), v 3.0

Resume treatment when the adverse reaction fully resolves, returns to baseline, or improves to Grade 1. Reinstitute GILOTRIF at a reduced dose, i.e., 10 mg per day less than the dose at which the adverse reaction occurred.

Permanently discontinue GILOTRIF for:

- Life-threatening bullous, blistering, or exfoliating skin lesions [see Warnings and Precautions (5.2)]
- Confirmed interstitial lung disease (ILD) [see Warnings and Precautions (5.3)]
- Severe drug-induced hepatic impairment [see Warnings and Precautions (5.4)]
- Gastrointestinal perforation [see Warnings and Precautions (5.5)]
- Persistent ulcerative keratitis [see Warnings and Precautions (5.6)]
- Symptomatic left ventricular dysfunction [see Adverse Reactions (6.1)]
- Severe or intolerable adverse reaction occurring at a dose of 20 mg per day

2.4 Dosage Modification for Pre-Existing Severe Renal Impairment

The recommended dosage of GILOTRIF in patients with pre-existing severe renal impairment (estimated glomerular filtration rate [eGFR*] 15 to 29 mL/min /1.73 m^2) is 30 mg orally once daily [see Use in Specific Populations (8.6), Clinical Pharmacology (12.3)].

* Use the Modification of Diet in Renal Disease [MDRD] formula to estimate eGFR.

2.5 Dosage Modifications for Drug Interactions

P-glycoprotein Inhibitors

Reduce GILOTRIF daily dose by 10 mg if not tolerated for patients who require therapy with a P-glycoprotein (P-gp) inhibitor. Resume the previous dose after discontinuation of the P-gp inhibitor as tolerated [see Drug Interactions (7), Clinical Pharmacology (12.3)].

P-glycoprotein Inducers

Increase GILOTRIF daily dose by 10 mg as tolerated for patients who require chronic therapy with a P-gp inducer. Resume the previous dose 2 to 3 days after discontinuation of the P-gp inducer [see Drug Interactions (7), Clinical Pharmacology (12.3)].

3 DOSAGE FORMS AND STRENGTHS

GILOTRIF is available as:

- 40 mg tablets: light blue, film-coated, round, biconvex, bevel-edged tablets debossed with "T40" on one side and the Boehringer Ingelheim company symbol on the other side.
- 30 mg tablets: dark blue, film-coated, round, biconvex, bevel-edged tablets debossed with "T30" on one side and the Boehringer Ingelheim company symbol on the other side.
- 20 mg tablets: white to slightly yellowish, film-coated, round, biconvex, bevel-edged tablets debossed with "T20" on one side and the Boehringer Ingelheim company symbol on the other side.

4 CONTRAINDICATIONS

None.

5 WARNINGS AND PRECAUTIONS

5.1 Diarrhea

Diarrhea has resulted in dehydration with or without renal impairment across the clinical experience; some cases were fatal. Grade 3-4 diarrhea occurred in 697 (16%) of the 4257 patients who received GILOTRIF across 44 clinical trials. In LUX-Lung 3, diarrhea occurred in 96% of patients treated with GILOTRIF (n=229), of which 15% were Grade 3 in severity and occurred within the first 6 weeks. Renal impairment as a consequence of diarrhea occurred in 6% of patients treated with GILOTRIF, of which 1.3% were Grade 3. In LUX-Lung 8, diarrhea occurred in 75% of patients treated with GILOTRIF (n=392), of which 10% were Grade 3 in severity and 0.8% were Grade 4 in severity. Renal impairment as a consequence of diarrhea occurred in 7% of patients treated with GILOTRIF, of which 2% were Grade 3 [see Adverse Reactions (6.1)].

For patients who develop prolonged Grade 2 diarrhea lasting more than 48 hours or greater than or equal to Grade 3 diarrhea, withhold GILOTRIF until diarrhea resolves to Grade 1 or less and resume GILOTRIF with appropriate dose reduction [see Dosage and Administration (2.3)]. Provide patients with an anti-diarrheal agent (e.g., loperamide) for self-administration at the onset of diarrhea and instruct patients to continue anti-diarrheal therapy until loose bowel movements cease for 12 hours.

5.2 Bullous and Exfoliative Skin Disorders

Grade 3 cutaneous reactions characterized by bullous, blistering, and exfoliating skin lesions, occurred in 0.2% of the 4257 patients who received GILOTRIF across clinical trials. In LUX-Lung 3, the overall incidence of cutaneous reactions consisting of rash, erythema, and acneiform rash was 90%, and the incidence of Grade 3 cutaneous reactions was 16%. In addition, the incidence of Grade 1-3 palmar-plantar erythrodysesthesia syndrome was 7%. In LUX-Lung 8, the overall incidence of cutaneous reactions consisting of rash, erythema, and acneiform rash was 70%, and the incidence of Grade 3 cutaneous reactions was 7%. In addition, the incidence of Grade 1-3 palmar-plantar erythrodysesthesia syndrome was 1.5% [see Adverse Reactions (6.1)].

Discontinue GILOTRIF in patients who develop life-threatening bullous, blistering, or exfoliating skin lesions. For patients who develop prolonged Grade 2 cutaneous adverse reactions lasting more than 7 days, intolerable Grade 2 cutaneous reactions, or Grade 3 cutaneous reactions, withhold GILOTRIF until the adverse reaction resolves to Grade 1 or less and resume GILOTRIF with appropriate dose reduction [see Dosage and Administration (2.3)].

Postmarketing cases consistent with toxic epidermal necrolysis (TEN) and Stevens Johnson syndrome (SJS) have been reported in patients receiving GILOTRIF. The cases of TEN and SJS bullous skin reactions result from a distinct and separate mechanism of toxicity than the bullous skin lesions secondary to the pharmacologic action of the drug on the epidermal growth factor receptor. Discontinue GILOTRIF if TEN or SJS is suspected [see Dosage and Administration (2.3)].

5.3 Interstitial Lung Disease

Interstitial lung disease or ILD-like adverse reactions (e.g., lung infiltration, pneumonitis, acute respiratory distress syndrome, or alveolitis allergic) occurred in 1.6% of the 4257 patients who received GILOTRIF across clinical trials; of these, 0.4% were fatal. The incidence of ILD appeared to be higher in Asian patients (2.3%; 38/1657) as compared to Whites (1.0%; 23/2241). In LUX-Lung 3, the incidence of Grade ≥3 ILD was 1.3% and resulted in death in 1% of GILOTRIF-treated patients. In LUX-Lung 8, the incidence of Grade ≥3 ILD was 0.9% and resulted in death in 0.8% of GILOTRIF-treated patients.

Withhold GILOTRIF during evaluation of patients with suspected ILD and discontinue GILOTRIF in patients with confirmed ILD [see Dosage and Administration (2.3)].

5.4 Hepatic Toxicity

In 4257 patients who received GILOTRIF across clinical trials, 9.7% had liver test abnormalities, of which 0.2% were fatal. In LUX-Lung 3, liver test abnormalities of any grade occurred in 17.5% of the patients treated with GILOTRIF, of which 3.5% had Grade 3-4 liver test abnormalities. In LUX-Lung 8, liver test abnormalities of any grade occurred in 6% of the patients treated with GILOTRIF, of which 0.2% had Grade 3-4 liver test abnormalities.

Obtain periodic liver testing in patients during treatment with GILOTRIF. Withhold GILOTRIF in patients who develop worsening of liver function [see Dosage and Administration (2.3)]. In patients who develop severe hepatic impairment while taking GILOTRIF, discontinue treatment.

5.5 Gastrointestinal Perforation

Gastrointestinal perforation, including fatal cases, has occurred with GILOTRIF. Gastrointestinal perforation has been reported in 0.2% of patients treated with GILOTRIF among 3213 patients across 17 randomized controlled clinical trials. Patients receiving concomitant corticosteroids, nonsteroidal anti-inflammatory drugs (NSAIDs) or anti-angiogenic agents, or patients with increasing age or who have an underlying history of gastrointestinal ulceration, underlying diverticular disease or bowel metastases may be at increased risk of perforation.

Permanently discontinue GILOTRIF in patients who develop gastrointestinal perforation [see Dosage and Administration (2.3)].

5.6 Keratitis

Keratitis, characterized as acute or worsening eye inflammation, lacrimation, light sensitivity, blurred vision, eye pain, and/or red eye occurred in 0.7% of patients treated with GILOTRIF among 4257 patients across clinical trials, of which 0.05% of patients experienced Grade 3 keratitis. Keratitis was reported in 2.2% patients in LUX-Lung 3, with Grade 3 in 0.4%. In LUX-Lung 8, keratitis was reported in 0.3% patients; there were no patients with ≥Grade 3 keratitis.

Withhold GILOTRIF during evaluation of patients with suspected keratitis, and if diagnosis of ulcerative keratitis is confirmed, interrupt or discontinue GILOTRIF [see Dosage and Administration (2.3)]. If keratitis is diagnosed, the benefits and risks of continuing treatment should be carefully considered. GILOTRIF should be used with caution in patients with a history of keratitis, ulcerative keratitis, or severe dry eye [see Adverse Reactions (6.1)]. Contact lens use is also a risk factor for keratitis and ulceration.

5.7 Embryo-Fetal Toxicity

Based on findings from animal studies and its mechanism of action, GILOTRIF can cause fetal harm when administered to a pregnant woman. Administration of afatinib to pregnant rabbits during organogenesis at exposures approximately 0.2 times the exposure in humans at the recommended dose of 40 mg daily resulted in embryotoxicity and, in rabbits showing maternal toxicity, increased abortions at late gestational stages. Advise pregnant women and females of reproductive potential of the potential risk to a fetus. Advise females of reproductive potential to use effective contraception during treatment and for at least 2 weeks after the last dose of GILOTRIF [see Use in Specific Populations (8.1, 8.3)].

6 ADVERSE REACTIONS

The following clinically significant adverse reactions are described elsewhere in the labeling:

- Diarrhea [see Warnings and Precautions (5.1)]
- Bullous and Exfoliative Skin Disorders [see Warnings and Precautions (5.2)]
- Interstitial Lung Disease [see Warnings and Precautions (5.3)]
- Hepatic Toxicity [see Warnings and Precautions (5.4)]
- Gastrointestinal Perforation [see Warnings and Precautions (5.5)]
- Keratitis [see Warnings and Precautions (5.6)]

6.1 Clinical Trials Experience

Because clinical trials are conducted under widely varying conditions, adverse reaction rates observed in the clinical trials of a drug cannot be directly compared to rates in the clinical trials of another drug and may not reflect the rates observed in practice.

The data in the Warnings and Precautions section reflect exposure to GILOTRIF for clinically significant adverse reactions in 4257 patients enrolled in LUX-Lung 3 (n=229) and LUX-Lung 8 (n=392), and 3636 patients with cancer enrolled in 42 studies of GILOTRIF administered alone or in combination with other anti-neoplastic drugs at GILOTRIF doses ranging from 10-70 mg daily or at doses 10-160 mg in other regimens. The mean exposure was 5.5 months. The population included patients with various cancers, the most common of which were NSCLC, breast, colorectal, brain, and head and neck.

The data described below reflect exposure to GILOTRIF as a single agent in LUX-Lung 3, a randomized, active-controlled trial conducted in patients with EGFR mutation-positive, metastatic NSCLC, and in LUX-Lung 8, a randomized, active-controlled trial in patients with metastatic squamous NSCLC progressing after platinum-based chemotherapy.

EGFR Mutation-Positive Metastatic NSCLC

The safety of GILOTRIF was evaluated in 229 EGFR-tyrosine kinase inhibitor-naïve patients with EGFR mutation-positive, metastatic non-squamous NSCLC enrolled in a randomized (2:1), multicenter, open-label trial (LUX-Lung 3). Patients received either GILOTRIF 40 mg daily until documented disease progression or intolerance to the therapy or pemetrexed 500 mg/m² followed after 30 minutes by cisplatin 75 mg/m² every three weeks for a maximum of six treatment courses. The median exposure was 11 months for patients treated with GILOTRIF and 3.4 months for patients treated with pemetrexed/cisplatin.

The overall trial population had a median age of 61 years; 61% of patients in the GILOTRIF arm and 60% of patients in the pemetrexed/cisplatin arm were younger than 65 years. A total of 64% of patients on GILOTRIF and 67% of pemetrexed/cisplatin patients were female. More than two-thirds of patients were from Asia (GILOTRIF 70%; pemetrexed/cisplatin 72%).

Serious adverse reactions were reported in 29% of patients treated with GILOTRIF. The most frequent serious adverse reactions reported in patients treated with GILOTRIF were diarrhea (6.6%); vomiting (4.8%); and dyspnea, fatigue, and hypokalemia (1.7% each). Fatal adverse reactions in GILOTRIF-treated patients in LUX-Lung 3 included pulmonary toxicity/ILD-like adverse reactions (1.3%), sepsis (0.43%), and pneumonia (0.43%).

Dose reductions due to adverse reactions were required in 57% of GILOTRIF-treated patients. The most frequent adverse reactions that led to dose reduction in the patients treated with GILOTRIF were diarrhea (20%), rash/acne (19%), paronychia (14%), and stomatitis (10%). Discontinuation of therapy in GILOTRIF-treated patients for adverse reactions was 14.0%. The most frequent adverse reactions that led to discontinuation in GILOTRIF-treated patients were diarrhea (1.3%), ILD (0.9%), and paronychia (0.9%).

Clinical trials of GILOTRIF excluded patients with an abnormal left ventricular ejection fraction (LVEF), i.e., below the institutional lower limit of normal. In LUX-Lung 3, all patients were evaluated for LVEF at screening and every 9 weeks thereafter in the GILOTRIF-treated group and as needed in the pemetrexed/cisplatin group. More GILOTRIF-treated patients (2.2%; n=5) experienced ventricular dysfunction (defined as diastolic dysfunction, left ventricular dysfunction, or ventricular dilation; all <Grade 3) compared to chemotherapy-treated patients (0.9%; n=1).

Tables 1 and 2 summarize common adverse reactions and laboratory abnormalities in LUX-Lung 3.

Table 1 Adverse Reactions Reported in ≥10% of GILOTRIF-Treated Patients in LUX-Lung 3*
Adverse Reaction | GILOTRIF n=229 |  | Pemetrexed/Cisplatin n=111
Adverse Reaction | All Grades (%) | Grade 3† (%) | All Grades (%) | Grade 3† (%)
Gastrointestinal disorders
Diarrhea | 96 | 15 | 23 | 2
Stomatitis^1 | 71 | 9 | 15 | 1
Cheilitis | 12 | 0 | 1 | 0
Skin and subcutaneous tissue disorders
Rash/acneiform dermatitis^2 | 90 | 16 | 11 | 0
Pruritus | 21 | 0 | 1 | 0
Dry skin | 31 | 0 | 2 | 0
Infections
Paronychia^3 | 58 | 11 | 0 | 0
Cystitis | 13 | 1 | 5 | 0
Respiratory, thoracic and mediastinal disorders
Epistaxis | 17 | 0 | 2 | 1
Rhinorrhea | 11 | 0 | 6 | 0
Investigations
Weight decreased | 17 | 1 | 14 | 1
General disorders and administration site conditions
Pyrexia | 12 | 0 | 6 | 0
Eye disorders
Conjunctivitis | 11 | 0 | 3 | 0
*NCI CTCAE v 3.0
†None of the adverse reactions in this table except stomatitis (one patient on GILOTRIF [0.4%]) were Grade 4 in severity.
^1Includes stomatitis, aphthous stomatitis, mucosal inflammation, mouth ulceration, oral mucosa erosion, mucosal erosion, mucosal ulceration
^2Includes acne, acne pustular, dermatitis, acneiform dermatitis, dermatosis, drug eruption, erythema, exfoliative rash, folliculitis, rash, rash erythematous, rash follicular, rash generalized, rash macular, rash maculo-papular, rash pruritic, rash pustular, skin disorder, skin erosion, skin exfoliation, skin fissures, skin lesion, skin reaction, skin toxicity, skin ulcer
^3Includes paronychia, nail infection, nail bed infection

Other clinically important adverse reactions observed in patients treated with GILOTRIF but that occurred at a higher incidence in pemetrexed/cisplatin-treated patients and not listed elsewhere in section 6 include: decreased appetite (29% Grades 1-4, 4% Grade 3), nausea (25% Grades 1-4, 4% Grade 3), and vomiting (23% Grades 1-4, 4% Grade 3).

Table 2 Laboratory Abnormalities Occurring in ≥10% of GILOTRIF Arm and at ≥2% Higher Incidence than in Chemotherapy Arm in LUX-Lung 3*
Laboratory Abnormality | GILOTRIF n=229 |  | Pemetrexed/Cisplatin n=111
Laboratory Abnormality | All Grades (%) | Grades 3-4 (%) | All Grades (%) | Grades 3-4 (%)
Increased alanine aminotransferase (ALT) | 54 | 2 | 27 | 1
Increased alkaline phosphate | 51 | 3 | 46 | 1
Decreased creatinine clearance | 49 | 2 | 47 | 1
Increased aspartate aminotransferase (AST) | 46 | 3 | 22 | 1
Decreased lymphocytes | 38 | 9 | 32 | 14
Decreased potassium | 30 | 8 | 11 | 3
Increased bilirubin | 16 | 1 | 8 | 0
*NCI CTCAE v 3.0

Previously Treated, Metastatic Squamous NSCLC

The safety of GILOTRIF was evaluated in 392 GILOTRIF-treated patients with metastatic squamous NSCLC enrolled in a randomized, multicenter, open-label trial (LUX-Lung 8). Patients were required to have received at least four cycles of platinum-based chemotherapy, ECOG Performance Status (PS) 0 or 1, and normal left ventricular ejection fraction (LVEF). Patients received GILOTRIF 40 mg once daily (n=392) or erlotinib 150 mg once daily (n=395). Treatment continued until documented disease progression or intolerance to the therapy. The median exposure was 2.1 months for patients treated with GILOTRIF, 15% were exposed for at least 6 months, and 5% were exposed for at least 12 months.

Among the 392 GILOTRIF-treated patients, the median age was 65 years, 53% were 65 years of age or older, 84% were male, 72% were White, 25% were Asian, ECOG PS 0 (32%) or 1 (68%).

Serious adverse reactions occurred in 44% of patients treated with GILOTRIF. The most frequent serious adverse reactions in patients treated with GILOTRIF were pneumonia (6.6%), diarrhea (4.6%), and dehydration and dyspnea (3.1% each). Fatal adverse reactions in GILOTRIF-treated patients included ILD (0.5%), pneumonia (0.3%), respiratory failure (0.3%), acute renal failure (0.3%), and general physical health deterioration (0.3%).

The most frequent adverse reactions that led to discontinuation in GILOTRIF-treated patients were diarrhea (4.1%) and rash/acne (2.6%).

Dose reductions due to adverse reactions were required in 27% of GILOTRIF-treated patients and discontinuation of GILOTRIF for adverse reactions was required for 20%. The most frequent adverse reactions that led to dose reduction in the patients treated with GILOTRIF were diarrhea (15%), rash/acne (5.9%), and stomatitis (3.1%).

Tables 3 and 4 summarize common adverse reactions and laboratory abnormalities in LUX-Lung 8.

Table 3 Adverse Reactions Reported in ≥10% of GILOTRIF-Treated Patients in LUX-Lung 8*
Adverse Reaction | GILOTRIF n=392 |  | Erlotinib n=395
Adverse Reaction | All Grades (%) | Grade 3-4 (%) | All Grades (%) | Grade 3-4 (%)
Gastrointestinal disorders
Diarrhea | 75 | 11 | 41 | 3
Stomatitis^1 | 30 | 4 | 11 | 1
Nausea | 21 | 2 | 16 | 1
Vomiting | 13 | 1 | 10 | 1
Skin and subcutaneous tissue disorders
Rash/acneiform dermatitis^2 | 70 | 7 | 70 | 11
Pruritus | 10 | 0 | 13 | 0
Metabolism and nutrition disorders
Decreased appetite | 25 | 3 | 26 | 2
Infections
Paronychia^3 | 11 | 1 | 5 | 0
*NCI CTCAE v 3.0
^1Includes stomatitis, aphthous stomatitis, mucosal inflammation, mouth ulceration, oral mucosa erosion, mucosal erosion, mucosal ulceration
^2Includes acne, dermatitis, acneiform dermatitis, eczema, erythema, exfoliative rash, folliculitis, rash, rash generalized, rash macular, rash maculo-papular, rash pruritic, rash pustular, skin exfoliation, skin fissures, skin lesion, skin reaction, skin toxicity, skin ulcer
^3Includes paronychia, nail infection, nail bed infection

Table 4 Laboratory Abnormalities Occurring in ≥10% of GILOTRIF Arm and at ≥2% Higher Incidence than in Erlotinib Arm in LUX-Lung 8*
Laboratory Abnormality | GILOTRIF n=392 |  | Erlotinib n=395
Laboratory Abnormality | All Grades (%) | Grades 3-4 (%) | All Grades (%) | Grades 3-4 (%)
Increased alkaline phosphate | 34 | 2 | 31 | 0
Decreased white blood cell count | 12 | 1 | 8 | 1
Decreased potassium | 11 | 1 | 8 | 1
*NCI CTCAE v 3.0

Other clinically important laboratory abnormalities observed in patients treated with GILOTRIF that are not listed in Table 4 are: increased alanine aminotransferase (10% Grade 1-4; 1% Grade 3-4), increased aspartate aminotransferase (7% Grade 1-4; 1% Grade 3-4), and increased bilirubin (3% Grade 1-4; 0 Grade 3-4).

Less Common Adverse Reactions

Other adverse reactions reported in patients treated with GILOTRIF in LUX-Lung 3 and LUX-Lung 8 include:

Skin and subcutaneous disorders: nail disorders occurred in 9.2% and 2.8% of patients, respectively.

6.2 Postmarketing Experience

The following adverse reactions have been identified during postapproval use of GILOTRIF. Because these reactions are reported voluntarily from a population of uncertain size, it is not always possible to reliably estimate their frequency or establish a causal relationship to drug exposure.

- Pancreatitis
- Toxic epidermal necrolysis/Stevens Johnson syndrome

7 DRUG INTERACTIONS

Effect of P-glycoprotein (P-gp) Inhibitors and Inducers

Concomitant taking of P-gp inhibitors (including but not limited to ritonavir, cyclosporine A, ketoconazole, itraconazole, erythromycin, verapamil, quinidine, tacrolimus, nelfinavir, saquinavir, and amiodarone) with GILOTRIF can increase exposure to afatinib [see Clinical Pharmacology (12.3)]. Reduce GILOTRIF daily dose as recommended [see Dosage and Administration (2.5)].

Concomitant taking of P-gp inducers (including but not limited to rifampicin, carbamazepine, phenytoin, phenobarbital, and St. John's wort) with GILOTRIF can decrease exposure to afatinib [see Clinical Pharmacology (12.3)]. Increase GILOTRIF daily dose as recommended [see Dosage and Administration (2.5)].

8 USE IN SPECIFIC POPULATIONS

8.1 Pregnancy

Risk Summary

Based on findings from animal studies and its mechanism of action [see Clinical Pharmacology (12.1)], GILOTRIF can cause fetal harm when administered to a pregnant woman. There are no available data on the use of GILOTRIF in pregnant women. Administration of afatinib to pregnant rabbits during organogenesis at exposures approximately 0.2 times the exposure in humans at the recommended dose of 40 mg daily resulted in embryotoxicity and, in rabbits showing maternal toxicity, increased abortions at late gestational stages (see Data). Advise a pregnant woman of the potential risk to a fetus.

The background risk of major birth defects and miscarriage for the indicated population is unknown. In the U.S. general population, the estimated background risk of major birth defects and miscarriage in clinically recognized pregnancies is 2% to 4% and 15% to 20%, respectively.

Data

Animal Data

In an embryo-fetal development study in rabbits, administration of afatinib to pregnant animals at doses of 5 mg/kg (approximately 0.2 times the exposure by AUC at the recommended human dose of 40 mg daily) or greater during the period of organogenesis caused increased post-implantation loss, and in animals showing maternal toxicity, abortion at late gestational stages. In the same study, at the high dose level of 10 mg/kg (approximately 0.7 times the exposure by AUC at the recommended human dose of 40 mg daily), there were reduced fetal weights, and increases in the incidence of runts, as well as visceral and dermal variations. In an embryo-fetal development study in rats, there were skeletal alterations consisting of incomplete or delayed ossifications and reduced fetal weight at a dose of 16 mg/kg (approximately twice the exposure based on AUC at the recommended human dose of 40 mg daily).

8.2 Lactation

Risk Summary

There are no data on the presence of afatinib in human milk or its effects on the breastfed infant or on milk production. Afatinib was present in the milk of lactating rats (see Data). Because of the potential for serious adverse reactions in breastfed infants from GILOTRIF, advise women not to breastfeed during treatment with GILOTRIF and for 2 weeks after the final dose.

Data

Afatinib was present in the milk of lactating rats at concentrations 80 and 150 times higher than those found in plasma at 1 and 6 hours after administration.

8.3 Females and Males of Reproductive Potential

Contraception

Females

GILOTRIF can cause fetal harm when administered to a pregnant woman. Advise females of reproductive potential to use effective contraception during treatment with GILOTRIF and for at least 2 weeks after the last dose of GILOTRIF [see Use in Specific Populations (8.1), Clinical Pharmacology (12.3)].

Infertility

Based on results from an animal fertility study, GILOTRIF may reduce fertility in females and males of reproductive potential. It is not known if the effects on fertility are reversible [see Nonclinical Toxicology (13.1)].

8.4 Pediatric Use

Safety and effectiveness of GILOTRIF in pediatric patients have not been established.

The safety and efficacy of afatinib were assessed, but not established, in a single-arm, open-label, multicenter trial [NCT02372006] which included 37 pediatric patients 2 to <17 years of age with recurrent/refractory solid tumors with known ErbB pathway deregulation who received 80% of the adult dose per body surface area. No new safety signals were observed in pediatric patients in this trial. In these 37 patients, the pharmacokinetic parameters were within range of values in adults.

8.5 Geriatric Use

LUX-Lung 3 did not include sufficient numbers of subjects aged 65 and over to determine whether they respond differently from younger subjects.

In LUX-Lung 8, 53% of the 398 patients randomized to receive afatinib were 65 years of age or older and 11% were 75 years or older. In an exploratory subgroup analysis of LUX-Lung 8, the hazard ratio for overall survival (OS) in patients less than 65 years old was 0.68 (95% CI: 0.55, 0.85) and in patients 65 years or older was 0.95 (95% CI: 0.76, 1.19). No overall differences in safety were observed between patients 65 years and older and younger patients.

8.6 Renal Impairment

Patients with severe renal impairment have a higher exposure to afatinib than patients with normal renal function. Administer GILOTRIF at a starting dose of 30 mg once daily in patients with severe renal impairment (eGFR 15 to 29 mL/min /1.73 m^2 as determined by Modification of Diet in Renal Disease formula) [see Dosage and Administration (2.4), Clinical Pharmacology (12.3)]. Adjustments to the starting dose of GILOTRIF are not necessary in patients with mild or moderate renal impairment (eGFR 30 to 89 mL/min /1.73 m^2). GILOTRIF has not been studied in patients with eGFR <15 mL/min/1.73 m^2 or on dialysis.

8.7 Hepatic Impairment

GILOTRIF has not been studied in patients with severe (Child Pugh C) hepatic impairment. Adjustments to the starting dose of GILOTRIF are not necessary in patients with mild (Child Pugh A) or moderate (Child Pugh B) hepatic impairment [see Clinical Pharmacology (12.3)]. Closely monitor patients with severe hepatic impairment and adjust GILOTRIF dose if not tolerated.

10 OVERDOSAGE

Overdose was reported in 2 healthy adolescents each of whom ingested 360 mg of GILOTRIF (as part of a mixed-drug ingestion) resulting in nausea, vomiting, asthenia, dizziness, headache, abdominal pain, and elevated amylase [<1.5 times upper limit of normal (ULN)]. Both subjects recovered.

11 DESCRIPTION

GILOTRIF tablets contain afatinib, a tyrosine kinase inhibitor which is a 4-anilinoquinazoline. Afatinib is presented as the dimaleate salt, with the chemical name 2-butenamide, N-[4-[(3-chloro-4-fluorophenyl)amino]-7-[[(3S)-tetrahydro-3-furanyl]oxy]-6-quinazolinyl]-4-(dimethylamino)-,(2E)-, (2Z)-2-butenedioate (1:2). Its structural formula is:

Afatinib dimaleate is a white to brownish yellow powder, water soluble and hygroscopic, with an empirical formula of C32H33ClFN5O11, and a molecular weight of 718.1 g/mol.

GILOTRIF tablets for oral administration are available in 40 mg, 30 mg, or 20 mg of afatinib (equivalent to 59.12 mg, 44.34 mg, or 29.56 mg afatinib dimaleate, respectively). The inactive ingredients of GILOTRIF are the following: Tablet Core: lactose monohydrate, microcrystalline cellulose, crospovidone, colloidal silicon dioxide, magnesium stearate and Coating: hypromellose, polyethylene glycol, titanium dioxide, talc, polysorbate 80, FD&C Blue No. 2 (40 mg and 30 mg tablets only).

12 CLINICAL PHARMACOLOGY

12.1 Mechanism of Action

Afatinib covalently binds to the kinase domains of EGFR (ErbB1), HER2 (ErbB2), and HER4 (ErbB4) and irreversibly inhibits tyrosine kinase autophosphorylation, resulting in downregulation of ErbB signaling. Certain mutations in EGFR, including non-resistant mutations in its kinase domain, can result in increased autophosphorylation of the receptor, leading to receptor activation, sometimes in the absence of ligand binding, and can support cell proliferation in NSCLC. Non-resistant mutations are defined as those occurring in exons constituting the kinase domain of EGFR that lead to increased receptor activation and where efficacy is predicted by 1) clinically meaningful tumor shrinkage with the recommended dose of afatinib and/or 2) inhibition of cellular proliferation or EGFR tyrosine kinase phosphorylation at concentrations of afatinib sustainable at the recommended dosage according to validated methods. The most commonly found of these mutations are exon 21 L858R substitutions and exon 19 deletions.

Afatinib demonstrated inhibition of autophosphorylation and/or in vitro proliferation of cell lines expressing wild-type EGFR and in those expressing selected EGFR exon 19 deletion mutations, exon 21 L858R mutations, or other less common non-resistant mutations, at afatinib concentrations achieved in patients. In addition, afatinib inhibited in vitro proliferation of cell lines overexpressing HER2.

Treatment with afatinib resulted in inhibition of tumor growth in nude mice implanted with tumors either overexpressing wild type EGFR or HER2 or in an EGFR L858R/T790M double mutant model.

12.2 Pharmacodynamics

Cardiac Electrophysiology

The effect of multiple doses of GILOTRIF (50 mg once daily) on the QTc interval was evaluated in an open-label, single-arm study in patients with relapsed or refractory solid tumors. No large changes in the mean QTc interval (i.e., >20 ms) were detected in the study.

12.3 Pharmacokinetics

Absorption

Following oral administration of GILOTRIF tablets, time to peak afatinib plasma concentrations (Tmax) is 2 to 5 hours. Maximum concentration (Cmax) and area under the concentration-time curve from time zero to infinity (AUC0-INF) values increased slightly more than dose proportional in the range of 20 to 50 mg. The geometric mean relative bioavailability of 20 mg GILOTRIF tablets was 92% as compared to an oral solution. Steady-state plasma concentrations are achieved within 8 days of repeat dosing of GILOTRIF resulting in an accumulation of 2.8-fold for AUC and 2.1-fold for Cmax.

Effect of Food

A high-fat meal decreased Cmax by 50% and AUC0-INF by 39% relative to the fasted condition [see Dosage and Administration (2.2)].

Distribution

In vitro binding of afatinib to human plasma proteins is approximately 95%.

Elimination

The elimination half-life of afatinib is 37 hours after repeat dosing in cancer patients.

Metabolism

Covalent adducts to proteins are the major circulating metabolites of afatinib and enzymatic metabolism of afatinib is minimal. The metabolites formed by CYP450-dependent reactions were approximately 9% of the total metabolic turnover in sandwich-cultured human hepatocytes. Approximately 2% of the afatinib dose was metabolized by FMO3; the CYP3A4-dependent N-demethylation was not detected.

Excretion

In humans, excretion of afatinib is primarily via the feces (85%) with 4% recovered in the urine following a single oral dose of [^14C]-labeled afatinib solution. The parent compound accounted for 88% of the recovered dose.

Specific Populations

Based on the population pharmacokinetic analysis, weight, gender, age, and race do not have a clinically important effect on exposure of afatinib.

Patients with Renal Impairment

A pharmacokinetic study was conducted in 14 subjects with normal (eGFR ≥90 mL/min/1.73 m^2) renal function, 8 subjects with moderate (eGFR 30 to 59 mL/min/1.73 m^2) and 8 subjects with severe (eGFR 15 to 29 mL/min/1.73 m^2) renal impairment. All subjects received a single 40 mg oral dose of GILOTRIF. The geometric mean AUCINF for afatinib was 50% higher in subjects with severe renal impairment and was 22% higher in subjects with moderate renal impairment as compared to subjects with normal renal function. Geometric mean Cmax was 22% higher in subjects with severe renal impairment and was comparable in subjects with moderate renal impairment to subjects with normal renal function [see Dosage and Administration (2.4), Use in Specific Populations (8.6)]. GILOTRIF has not been studied in patients with eGFR <15 mL/min/1.73 m^2 or on dialysis.

Patients with Hepatic Impairment

Mild (Child Pugh A) or moderate (Child Pugh B) hepatic impairment had no influence on the afatinib exposure following a single dose of GILOTRIF. Subjects with severe (Child Pugh C) hepatic impairment have not been studied [see Use in Specific Populations (8.7)].

Drug Interactions Studies

Clincial Studies

Effect of P-gp Inhibitors and Inducers on Afatinib: The effect of ritonavir dosing time relative to a single oral dose of GILOTRIF was evaluated in healthy subjects taking 40 mg of GILOTRIF alone as compared to those after ritonavir (200 mg twice daily for 3 days) co-administration at 6 hours after GILOTRIF administration. The relative bioavailability for AUC0-INF and Cmax of afatinib was 119% and 104% when co-administered with ritonavir, and 111% and 105% when ritonavir was administered 6 hours after taking GILOTRIF. In another study, when ritonavir (200 mg twice daily for 3 days) was administered 1 hour before a 20 mg single dose of GILOTRIF, exposure to afatinib increased by 48% for AUC0-INF and 39% for Cmax [see Drug Interactions (7)].

Pre-treatment with a potent inducer of P-gp, rifampicin (600 mg once daily for 7 days) decreased the plasma exposure to afatinib by 34% (AUC0-INF) and 22% (Cmax) [see Drug Interactions (7)].

In Vitro Studies

Effect of Afatinib on P-gp: Based on in vitro data, afatinib is an inhibitor of P-gp.

Interaction of Afatinib with BCRP: Based on in vitro data, afatinib is a substrate and an inhibitor of the transporter BCRP.

Effect of Afatinib on CYP450 Enzymes: Afatinib is not an inhibitor or an inducer of CYP450 enzymes (CYP1A2, 2B6, 2C8, 2C9, 2C19, and 3A4) in cultured primary human hepatocytes.

13 NONCLINICAL TOXICOLOGY

13.1 Carcinogenesis, Mutagenesis, Impairment of Fertility

Carcinogenicity studies have not been conducted with afatinib.

A marginal response to afatinib was observed in a single tester strain of a bacterial (Ames) mutagenicity assay. No mutagenic or genotoxic potential was identified in an in vitro chromosomal aberration test at non-cytotoxic concentrations as well as in the in vivo bone marrow micronucleus assay, the in vivo Comet assay, and an in vivo 4-week oral mutation study in the Muta™ Mouse.

In a dedicated fertility study, male and female rats received afatinib daily by oral administration at doses of 4, 6, or 8 mg/kg. In males at doses of 6 mg/kg (approximately equal to the exposure by AUC in patients at the recommended human dose of 40 mg daily) or greater, there was an increase in the incidence of low or no sperm count, though overall fertility was not affected; decreases in sperm count were supported by findings of increased apoptosis in the testes and atrophy in the seminal vesicles and the prostate in general toxicology studies. In females at the high dose of 8 mg/kg (approximately 0.63 times the exposure by AUC in patients at the recommended human dose of 40 mg daily), there was a mild decrease in the number of corpora lutea along with a mild increase in post-implantation loss due to early resorptions. In a 4-week general toxicology study, female rats had decreases in ovarian weights at all dose levels; organ weight had not fully recovered by the end of a 2-week recovery period.

14 CLINICAL STUDIES

14.1 EGFR Mutation-Positive, Metastatic NSCLC

The efficacy of GILOTRIF for the first-line treatment of patients with EGFR mutation-positive, metastatic [Stage IV and Stage IIIb with pleural and/or pericardial effusion as classified by the American Joint Commission on Cancer (AJCC, 6th edition)] NSCLC was established in a randomized, multicenter, open-label trial (LUX-Lung 3 [NCT00949650]). Patients were randomized (2:1) to receive GILOTRIF 40 mg orally once daily (n=230) or intravenous pemetrexed (500 mg/m^2) plus cisplatin (75 mg/m^2) once every 21 days for up to 6 cycles (n=115). Randomization was stratified according to EGFR mutation category (exon 19 deletion vs exon 21 L858R vs other) and race (Asian vs non-Asian). The major efficacy outcome was progression-free survival (PFS) as assessed by an independent review committee (IRC). Other efficacy outcomes included overall response rate (ORR) and OS. EGFR mutation status was prospectively determined for screening and enrollment of patients by a clinical trial assay (CTA). Tumor samples from 264 patients (178 randomized to GILOTRIF and 86 patients randomized to chemotherapy) were tested retrospectively by the companion diagnostic therascreen® EGFR RGQ PCR Kit, which is FDA-approved for selection of patients for GILOTRIF treatment.

Among the patients randomized, 65% were female, median age was 61 years, baseline ECOG performance status (PS) was 0 (39%) or 1 (61%), 26% were White and 72% were Asian. The majority of the patients had a tumor sample with an EGFR mutation categorized by the CTA as either exon 19 deletion (49%) or exon 21 L858R substitution (40%), while the remaining 11% had other mutations.

A statistically significant improvement in PFS as determined by the IRC was demonstrated for patients randomized to GILOTRIF compared with those randomized to chemotherapy. See Table 5 and Figure 1. There was no statistically significant difference for OS between the treatment arms at the final pre-planned analysis.

Table 5 Efficacy Results in LUX-Lung 3
 | GILOTRIF (N=230) | Pemetrexed/Cisplatin (N=115)
Progression-Free Survival by IRC
Number of Deaths or Progressions, N (%) | 152 (66.1%) | 69 (60.0%)
Median Progression-Free Survival (months) | 11.1 | 6.9
95% CI | (9.6, 13.6) | (5.4, 8.2)
HR (95% CI) | 0.58 (0.43, 0.78)
Stratified Log-Rank Test p-value* | <0.001
Overall Survival
Number of Deaths, N (%) | 140 (60.9%) | 73 (63.5%)
Median Overall Survival (months) | 28.2 | 28.2
95% CI | (24.6, 33.6) | (20.7, 33.2)
HR (95% CI) | 0.88 (0.66, 1.17)
Stratified Log-Rank Test p-value* | 0.39
Overall Response Rate (CR + PR) by IRC
N (%) | 116 (50.4%) | 22 (19.1%)
Response Duration
Median (months) | 12.5 | 6.7
*Stratified by EGFR mutation status and race.
HR=hazard ratio; CR=complete response; PR=partial response

Figure 1 Kaplan-Meier Curve for PFS by Independent Review by Treatment Group in LUX-Lung 3

Pre-specified exploratory subgroup analyses were conducted according to the stratification factor of EGFR mutation category. See Figure 2 and text below Figure 2.

Figure 2 Forest Plots of PFS and OS by EGFR Mutation Subgroups in LUX-Lung 3

Overall Response Rate in Other EGFR Mutations

The efficacy of GILOTRIF in patients with NSCLC harboring non-resistant EGFR mutations (S768I, L861Q, and G719X) other than exon 19 deletions or exon 21 L858R substitutions was evaluated in a pooled analysis of such patients enrolled in one of three clinical trials (LUX-Lung 2 [NCT00525148], LUX-Lung 3 [NCT00949650], and LUX-Lung 6 [NCT01121393]).

- LUX-Lung 2 was a single arm, multicenter study of afatinib 40 or 50 mg orally once daily until disease progression or intolerable side effects. EGFR status was determined by bi-directional Sanger sequencing of tumor tissue.
- LUX-Lung 3 was a randomized, multicenter study comparing treatment with afatinib 40 mg orally once daily to intravenous cisplatin 75 mg/m^2 plus pemetrexed 500 mg/m^2 every 21 days for up to 6 cycles. EGFR status was determined by the therascreen® EGFR RGQ PCR Kit.
- LUX-Lung 6 was a randomized, multicenter study comparing treatment with afatinib 40 mg to intravenous gemcitabine 1000 mg/m^2 on day 1 and day 8 plus cisplatin 75 mg/m^2 on day 1 of a 3-week schedule for up to 6 cycles. EGFR status was determined by the therascreen® EGFR RGQ PCR Kit.

Among the 75 GILOTRIF-treated patients with uncommon EGFR mutations, 32 patients had a non-resistant EGFR mutation. Among the 32 patients with a confirmed non-resistant EGFR mutation, the median age was 60.5 years (range 32-79), 66% were female, 97% were Asian, 3% were other races, 38% had an ECOG PS of 0, 63% had an ECOG PS 1, 66% were never smokers, 28% were former smokers, and 6% were current smokers. Baseline disease characteristics were 97% Stage IV disease, 3% Stage IIIb disease, and 88% had received no prior systemic therapy for advanced or metastatic disease.

The number of patients, the number of responders, and durations of response in subgroups defined by identified mutation(s) are summarized in Table 6.

Table 6 IRC-Assessed Responses in Patients with NSCLC Harboring EGFR Mutations G719X, L861Q, and/or S768I from LUX-Lung 2, LUX-Lung 3, and LUX-Lung 6
EGFR Mutation | Number of GILOTRIF Treated Patients (N=32) | Number of Confirmed Responses (N=21) | Duration of Response (months) (N=21)
S768I | 1 | 1 | 37.3
S768I and G719X | 5 | 4 | 4.1, 13.2, 15.2, 29.5+
S768I and L858R | 2 | 1 | 34.5+
G719X | 8 | 6 | 5.7+, 8.1, 9.6, 23.5+, 25.2, 31.8+
G719X and L861Q | 3 | 2 | 2.8+, 6.8
L861Q | 12 | 7 | 2.8, 4.0, 4.1, 8.3+, 12.9, 15.2, 20.6
L861Q and Del 19 | 1 | 0 | NA
+ response ongoing at time of censoring

14.2 Previously Treated, Metastatic Squamous NSCLC

The efficacy and safety of GILOTRIF were demonstrated in a randomized, multicenter, open-label, active-controlled study (LUX-Lung 8 [NCT01523587]). Patients were required to have histologically documented, metastatic squamous NSCLC and have experienced disease progression following an adequate course (≥4 cycles) of a platinum-based doublet chemotherapy regimen. Patients were randomized (1:1) to receive GILOTRIF 40 mg or erlotinib 150 mg orally once daily until progression. Randomization was stratified by region (Eastern Asia vs other). The major efficacy outcome measure was PFS as assessed by an IRC using RECIST v 1.1. Additional efficacy outcome measures were OS and ORR as assessed by IRC.

Baseline patient demographics of the 795 patients were: median age 64 years (range: 35 to 88); 73% White; 24% Asian; 84% male; 33% ECOG PS 0 and 67% ECOG PS 1; and 95% current or former smokers. With regard to tumor characteristics, 96% had squamous cell histology and 3.5% had mixed cell histology. All patients received platinum-based doublet therapy.

The study demonstrated a statistically significant improvement in PFS and OS for patients randomized to GILOTRIF as compared with erlotinib (see Table 7 and Figure 3).

Table 7 Efficacy Results in LUX-Lung 8
 | GILOTRIF | Erlotinib
Overall Survival
 | N=398 | N=397
Number of Deaths, N (%) | 307 (77%) | 325 (82%)
Median overall survival (months) | 7.9 | 6.8
95% CI | (7.2, 8.7) | (5.9, 7.8)
HR (95% CI) | 0.81 (0.69, 0.95)
p-value* | 0.008
Progression-Free Survival (PFS) by IRC
 | N=335 | N=334
Number of Events, N (%) | 202 (60%) | 212 (64%)
Median PFS (months) | 2.4 | 1.9
95% CI | (1.9, 2.9) | (1.9, 2.2)
HR (95% CI) | 0.82 (0.68, 0.998)
p-value* | 0.0427
Overall Response Rate (ORR) by IRC
 | N=335 | N=334
ORR | 3% | 2%
(95% CI) | (1.7, 5.8) | (0.8, 4.3)
*Log-rank test stratified by region.
HR=hazard ratio

Figure 3 Kaplan-Meier Curves of Overall Survival in LUX-Lung 8

16 HOW SUPPLIED/STORAGE AND HANDLING

GILOTRIF tablets are available as follows:

40 mg: light blue, film-coated, round, biconvex, bevel-edged tablets debossed with "T40" on one side and the Boehringer Ingelheim company symbol on the other side.

Unit of use bottles of 30

NDC: 0597-0138-30

30 mg: dark blue, film-coated, round, biconvex, bevel-edged tablets debossed with "T30" on one side and the Boehringer Ingelheim company symbol on the other side.

Unit of use bottles of 30

NDC: 0597-0137-30

20 mg: white to slightly yellowish, film-coated, round, biconvex, bevel-edged tablets debossed with "T20" on one side and the Boehringer Ingelheim company symbol on the other side.

Unit of use bottles of 30

NDC: 0597-0141-30

Storage

Store at 20°C to 25°C (68°F to 77°F); excursions permitted to 15° to 30°C (59° to 86°F) [see USP Controlled Room Temperature]. Dispense medication in the original container to protect from exposure to high humidity and light.

17 PATIENT COUNSELING INFORMATION

Advise the patient to read the FDA-approved patient labeling (Patient Information).

Diarrhea

Advise patients that diarrhea occurs in nearly all patients who receive GILOTRIF. Inform patients that diarrhea may result in dehydration and renal impairment if not treated. Advise patients to notify their physician if diarrhea develops and to seek medical attention promptly for severe or persistent diarrhea [see Warnings and Precautions (5.1) and Adverse Reactions (6.1)].

Bullous and Exfoliative Skin Disorders

Advise patients to minimize sun exposure with protective clothing and use of sunscreen while taking GILOTRIF [see Warnings and Precautions (5.2)].

Interstitial Lung Disease

Advise patients to immediately report any new or worsening lung symptoms, or any combination of the following symptoms: trouble breathing or shortness of breath, cough, fever [see Warnings and Precautions (5.3)].

Hepatic Toxicity

Advise patients that they will need to undergo liver function monitoring periodically. Advise patients to immediately report any symptoms of a liver problem [e.g., skin or the whites of eyes turn yellow, urine turns dark or brown (tea colored), pain on the right side of stomach, bleeds or bruises more easily than normal, lethargy] [see Warnings and Precautions (5.4)].

Gastrointestinal Perforation

Advise patients that GILOTRIF can increase the risk of gastrointestinal perforation and to seek immediate medical attention for severe abdominal pain [see Warnings and Precautions (5.5)].

Keratitis

Advise patients to immediately report eye problems (e.g., eye pain, swelling, redness, blurred vision, or other vision changes) [see Warnings and Precautions (5.6)].

Left Ventricular Dysfunction

Advise patients to contact a healthcare professional immediately for any of the following: new onset or worsening shortness of breath or exercise intolerance, cough, fatigue, swelling of the ankles/legs, palpitations, or sudden weight gain [see Dosage and Administration (2.3) and Adverse Reactions (6.1)].

Instructions for Taking GILOTRIF

Advise patients to take GILOTRIF on an empty stomach at least 1 hour before or 2 hours after eating [see Dosage and Administration (2.2)]. Advise patients not to take a missed dose within 12 hours of the next dose.

Embryo-Fetal Toxicity

Advise pregnant women and females of reproductive potential that GILOTRIF can result in fetal harm. Advise female patients to contact their healthcare provider with a known or suspected pregnancy. Advise females of reproductive potential to use effective contraception during treatment with GILOTRIF and for at least 2 weeks after the last dose of GILOTRIF [see Use in Specific Populations (8.1, 8.3)].

Lactation

Advise women not to breastfeed during treatment with GILOTRIF and for 2 weeks after the last dose of GILOTRIF [see Use in Specific Populations (8.2)].

Infertility

Advise females and males of reproductive potential of the potential for reduced fertility from GILOTRIF [see Use in Specific Populations (8.3)].

Distributed by:
Boehringer Ingelheim Pharmaceuticals, Inc.
Ridgefield, CT 06877 USA

Licensed from:
Boehringer Ingelheim International GmbH

GILOTRIF is a registered trademark of and used under license from Boehringer Ingelheim International GmbH.

The other brands listed are trademarks of their respective owners and are not trademarks of Boehringer Ingelheim Pharmaceuticals, Inc.

Copyright © 2022 Boehringer Ingelheim International GmbH
ALL RIGHTS RESERVED

COL9594AD042022

SPL9596A

Patient Information
GILOTRIF® (JEE-loh-trif)
(afatinib tablets)

What is GILOTRIF?
GILOTRIF is a prescription medicine that is used to treat people with non-small cell lung cancer (NSCLC) that:

- has certain (non-resistant) abnormal epidermal growth factor receptor (EGFR) gene(s). Your healthcare provider will perform a test to make sure that GILOTRIF is right for you.
- has spread to other parts of the body (metastatic), and
- has not been previously treated for metastatic lung cancer

It is not known if GILOTRIF is safe and effective in treating people with lung cancer that has resistant abnormal EGFR genes.
or
is used to treat people with squamous cell lung cancer that:

- has spread to other parts of the body, and
- has been previously treated with chemotherapy that contains platinum.

It is not known if GILOTRIF is safe and effective in children.

Before you take GILOTRIF, tell your healthcare provider about all of your medical conditions, including if you:

- have kidney or liver problems
- have lung or breathing problems other than lung cancer
- have a history of an ulcer, a tear (perforation) in your stomach or intestine, or diverticular disease (inflammation) in parts of your large intestine. See "What are the possible side effects of GILOTRIF?"
- have a history of severe dry eye or any other eye problems. Tell your healthcare provider if you wear contact lenses.
- have heart problems
- are pregnant or plan to become pregnant. GILOTRIF can harm your unborn baby.
  - Females who are able to become pregnant should use effective birth control during treatment with GILOTRIF and for at least 2 weeks after your last dose of GILOTRIF. Talk to your healthcare provider about birth control methods that may be right for you.
  - Tell your healthcare provider right away if you become pregnant or think you are pregnant during treatment with GILOTRIF.
- are breastfeeding or plan to breastfeed. It is not known if GILOTRIF passes into your breast milk. Do not breastfeed during treatment with GILOTRIF and for 2 weeks after your last dose of GILOTRIF. Talk to your healthcare provider about the best way to feed your baby if you take GILOTRIF.

Tell your healthcare provider about all the medicines you take, including prescription and over-the-counter medicines, vitamins, and herbal supplements. GILOTRIF may affect the way other medicines work, and other medicines may affect the way GILOTRIF works. Taking certain medicines with GILOTRIF may increase your risk of developing a tear (perforation) in your stomach or intestine. See "What are the possible side effects of GILOTRIF?"
Know the medicines you take. Keep a list of them to show your healthcare provider or pharmacist when you get a new medicine.

How should I take GILOTRIF?

- Take GILOTRIF exactly as your healthcare provider tells you to take it.
- Your healthcare provider will tell you how many GILOTRIF tablets to take and when to take them. Do not change your dose or stop GILOTRIF unless your healthcare provider tells you to.
- Take GILOTRIF on an empty stomach at least 1 hour before a meal or 2 hours after a meal.
- If you miss a dose of GILOTRIF, take it as soon as you remember. If it is within 12 hours of your next dose, skip the dose and just take your next dose at your regular time. Do not take 2 doses of GILOTRIF at the same time.
- If you take too much GILOTRIF, call your healthcare provider or go to the nearest hospital emergency room right away.

What should I avoid while taking GILOTRIF?
Limit your time in the sun. GILOTRIF can make your skin sensitive to sunlight. You could get or have worsening rash or acne. You could get a severe sunburn. Use sunscreen and wear a hat and clothes that cover your skin if you have to be in sunlight during treatment with GILOTRIF.

What are the possible side effects of GILOTRIF?
GILOTRIF may cause serious side effects, including:

- diarrhea. Diarrhea is common with GILOTRIF and may sometimes be severe. Severe diarrhea can cause loss of too much body fluid (dehydration) and kidney problems that can sometimes lead to death. During your treatment with GILOTRIF, your healthcare provider should prescribe medicines to treat diarrhea. Take this medicine exactly as your healthcare provider tells you to. Tell your healthcare provider if you have diarrhea. Get medical attention right away if your diarrhea does not go away or becomes severe.
- skin reactions. GILOTRIF can cause redness, rash, and acne. It is important to get treatment for skin reactions as soon as you notice them. Take medicines to help skin reactions exactly as your healthcare provider tells you to. Get medical attention right away if you develop severe skin reactions such as peeling or blistering of the skin, or blisters in your mouth.
- lung or breathing problems. GILOTRIF may cause inflammation of the lung that may lead to death. Symptoms may be similar to those symptoms from lung cancer. Tell your healthcare provider right away if you have any new or worsening lung problems, or any combination of the following symptoms: trouble breathing or shortness of breath, cough, or fever.
- liver problems. GILOTRIF can cause liver problems that can sometimes lead to death. Tell your healthcare provider right away if you have any symptoms of a liver problem which may include:
  - yellowing of your skin or the white part of your eyes (jaundice)
  - dark or brown (tea colored) urine
  - pain on the upper right side of your stomach area (abdomen)
  - bleeding or bruising more easily than normal
  - feeling very tired
  Your healthcare provider will do blood tests to check your liver function during your treatment with GILOTRIF.
- tear (perforation) in your stomach or intestine. Tears in your stomach or intestine can happen with GILOTRIF and can sometimes lead to death. Your risk of developing a tear in your stomach or intestine may be increased if you:
  - take certain medicines with GILOTRIF including: corticosteroids, nonsteroidal anti-inflammatory drugs (NSAIDs), and certain other medicines.
  - have a history of stomach or intestinal ulcers, or if you have had diverticular disease (inflammation in parts of the large intestine).
  Get medical help right away if you develop severe stomach-area (abdomen) pain during treatment with GILOTRIF.
- eye problems. Tell your healthcare provider right away if you have symptoms of eye problems which may include:

- eye pain, swelling, redness, or tearing
- blurred vision

- sensitivity to light
- other changes in your vision

- heart problems. Tell your healthcare provider right away if you have symptoms of a heart problem which may include:

- new or worsening shortness of breath while at rest or with activity
- cough
- tiredness

- swelling of your ankles, feet, or legs
- feeling that your heart is pounding or racing (palpitations)
- sudden weight gain

Your healthcare provider may change your dose, temporarily stop or permanently stop treatment with GILOTRIF if you have certain side effects.
The most common side effects of GILOTRIF include:

- diarrhea
- rash
- acne
- mouth sores

- nail inflammation
- dry skin
- decreased appetite

- nausea
- vomiting
- itching

GILOTRIF may cause decreased fertility in females and males. This may affect your ability to have a child. Talk to your healthcare provider if this is a concern for you.
Tell your healthcare provider if you have any side effect that bothers you or that does not go away.
These are not all of the possible side effects of GILOTRIF. For more information, ask your healthcare provider or pharmacist. Call your doctor for medical advice about side effects. You may report side effects to FDA at 1-800-FDA-1088.

How should I store GILOTRIF?

- Store GILOTRIF at room temperature between 68°F to 77°F (20°C to 25°C).
- Keep GILOTRIF in the original container and keep the container tightly closed.
- Keep GILOTRIF away from moisture and light.
- Safely throw away (discard) any GILOTRIF that is out of date or no longer needed.

Keep GILOTRIF and all medicines out of the reach of children.

General information about GILOTRIF
Medicines are sometimes prescribed for purposes other than those listed in a Patient Information leaflet. Do not use GILOTRIF for a condition for which it was not prescribed. Do not give GILOTRIF to other people, even if they have the same symptoms you have. It may harm them. You can ask your healthcare provider or pharmacist for information about GILOTRIF that is written for health professionals.

What are the ingredients in GILOTRIF?
Active ingredient: afatinib
Inactive ingredients: Tablet Core: lactose monohydrate, microcrystalline cellulose, crospovidone, colloidal silicon dioxide, magnesium stearate. Tablet Coating: hypromellose, polyethylene glycol, titanium dioxide, talc, polysorbate 80, FD&C Blue No. 2 (40 mg and 30 mg tablets only).

Distributed by: Boehringer Ingelheim Pharmaceuticals, Inc. Ridgefield, CT 06877 USA
Licensed from: Boehringer Ingelheim International GmbH
GILOTRIF is a registered trademark of and used under license from Boehringer Ingelheim International GmbH.
Copyright © 2022 Boehringer Ingelheim International GmbH ALL RIGHTS RESERVED
COL9594AD042022
For more information about GILOTRIF, including current prescribing information, go to www.gilotrif.com, scan the code, or call Boehringer Ingelheim Pharmaceuticals, Inc. at 1-800-542-6257.

This Patient Information has been approved by the U.S. Food and Drug Administration.

Revised: April 2022

PRINCIPAL DISPLAY PANEL - 20 mg Tablet Bottle Carton

NDC 0597-0141-30

GILOTRIF®
(afatinib tablets)

20 mg*

Attention: Dispense and Store
Medication in the Original Container
to Protect from Light and Humidity.

Recommended Dosage: See Prescribing
Information.

30 tablets

Boehringer
Ingelheim

Rx only

PRINCIPAL DISPLAY PANEL - 30 mg Tablet Bottle Carton

NDC 0597-0137-30

GILOTRIF®
(afatinib tablets)

30 mg*

Attention: Dispense and Store
Medication in the Original Container
to Protect from Light and Humidity.

Recommended Dosage: See Prescribing
Information.

30 tablets

Boehringer
Ingelheim

Rx only

PRINCIPAL DISPLAY PANEL - 40 mg Tablet Bottle Carton

NDC 0597-0138-30

GILOTRIF®
(afatinib tablets)

40 mg*

Attention: Dispense and Store
Medication in the Original Container
to Protect from Light and Humidity.

Recommended Dosage:
See Prescribing Information.

30 tablets

Boehringer
Ingelheim

Rx only